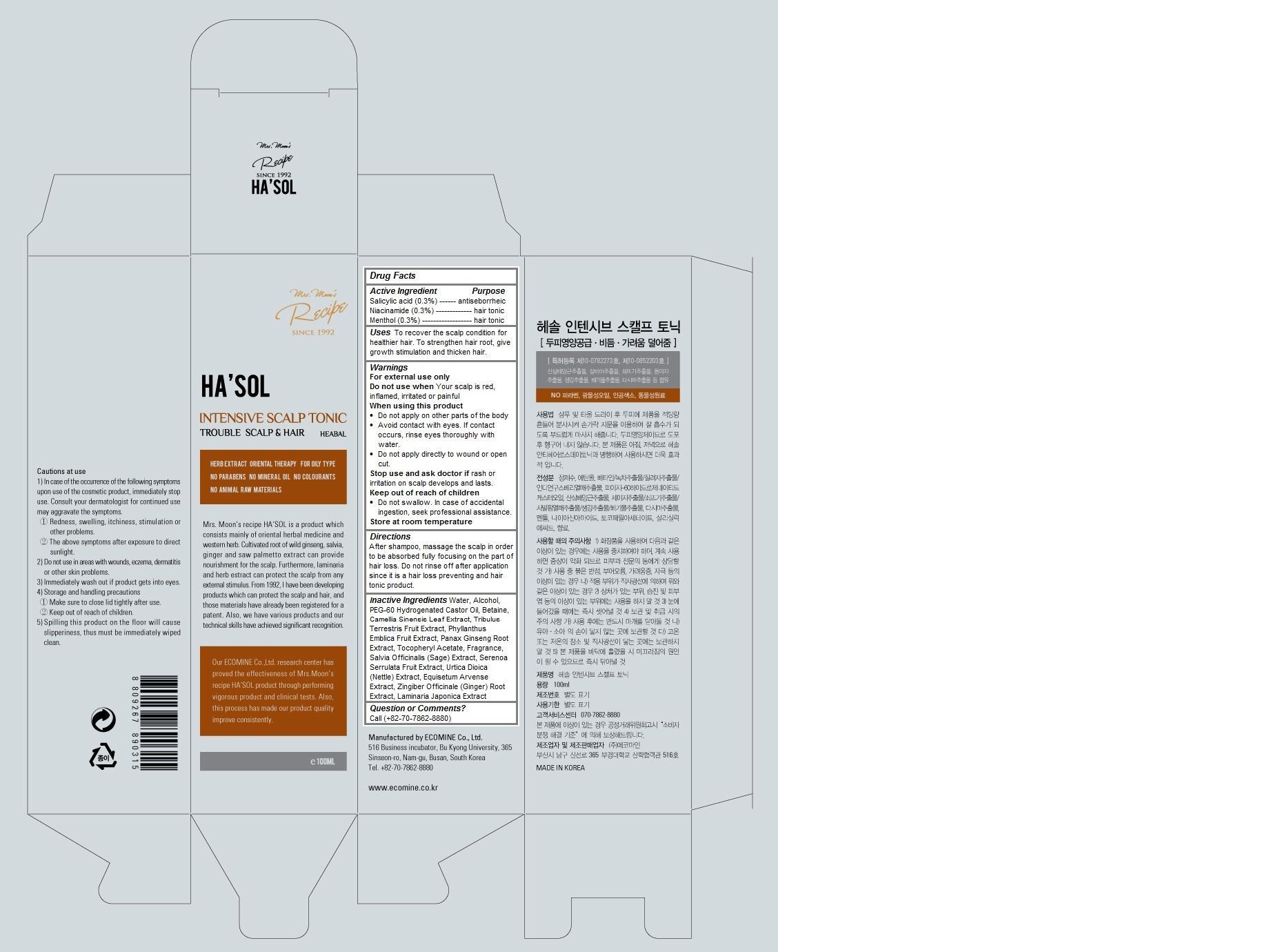 DRUG LABEL: HASOL Intensive Scalp Tonic
NDC: 51270-120 | Form: LIQUID
Manufacturer: ECOMINE Co., Ltd.
Category: otc | Type: HUMAN OTC DRUG LABEL
Date: 20140820

ACTIVE INGREDIENTS: SALICYLIC ACID 0.3 1/100 mL; NIACINAMIDE 0.3 1/100 mL; MENTHOL 0.3 1/100 mL
INACTIVE INGREDIENTS: WATER; ALCOHOL; PEG-60 HYDROGENATED CASTOR OIL; BETAINE; GREEN TEA LEAF; TRIBULUS TERRESTRIS FRUIT; PHYLLANTHUS EMBLICA FRUIT; ASIAN GINSENG; .ALPHA.-TOCOPHEROL ACETATE; SALVIA OFFICINALIS WHOLE; SAW PALMETTO; URTICA DIOICA LEAF; EQUISETUM ARVENSE BRANCH; GINGER; LAMINARIA JAPONICA

HA'SOL Intensive Scalp Tonic